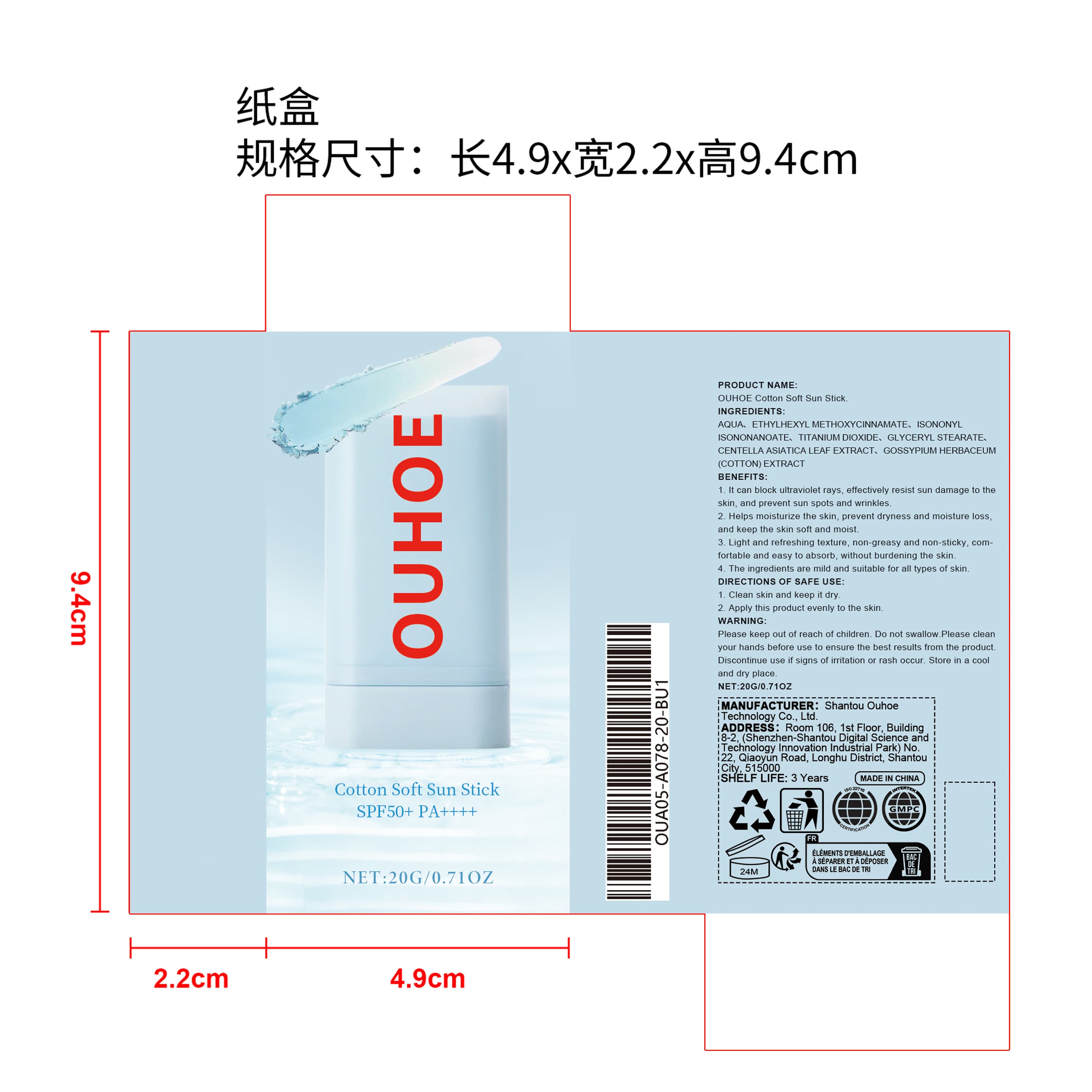 DRUG LABEL: OUHOE Cotton Soft Sun Stick
NDC: 85163-014 | Form: CREAM
Manufacturer: Shantou Ouhoe Technology Co., Ltd.
Category: otc | Type: HUMAN OTC DRUG LABEL
Date: 20251206

ACTIVE INGREDIENTS: GOSSYPIUM HERBACEUM (COTTON) SEED OIL 0.004 mg/20 mg; CENTELLA ASIATICA LEAF 0.06 mg/20 mg
INACTIVE INGREDIENTS: AQUA 17.636 mg/20 mg; TITANIUM DIOXIDE 0.2 mg/20 mg; ISONONYL ISONONANOATE 0.8 mg/20 mg; GLYCERYL STEARATE 0.3 mg/20 mg; ETHYLHEXYL METHOXYCINNAMATE 1 mg/20 mg

ACTIVE INGREDIENT

PCENTELLA ASIATICA LEAF EXTRACT、GOSSYPIUM HERBACEUM (COTTON) EXTRACT

PURPOSE

1. It can block ultraviolet rays, effectively resist sun damage to the skin, and prevent sun spots and wrinkles.

2. Helps moisturize the skin, prevent dryness and moisture loss, and keep the skin soft and moist.

3. Light and refreshing texture, non-greasy and non-sticky, comfortable and easy to absorb, without burdening the skin.

4. The ingredients are mild and suitable for all types of skin.

WHEN USING

1. Clean skin and keep it dry

2. Apply this product evenly to the skin

WARNINGS

Please keep out of reach of children. Do not swallow.Please clean your hands before use to ensure the best results from the product. Discontinue use if signs of irritation or rash occur. Store in a cool and dry place.

STOP USE

Discontinue use if signs of irritation or rash occur.

DO NOT USE

Discontinue use if signs of irritation or rash occur.

KEEP OUT OF REACH OF CHILDREN

Please keep out of reach of children. Do not swallow.

STORAGE AND HANDLING

Store in a cool and dry place.

INACTIVE INGREDIENT

AQUA、ETHYLHEXYL METHOXYCINNAMATE、ISONONYL ISONONANOATE、TITANIUM DIOXIDE、GLYCERYL STEARATE

INDICATIONS AND USAGE

1. Clean skin and keep it dry

2. Apply this product evenly to the skin

DOSAGE AND ADMINISTRATION

1. Clean skin and keep it dry

2. Apply this product evenly to the skin